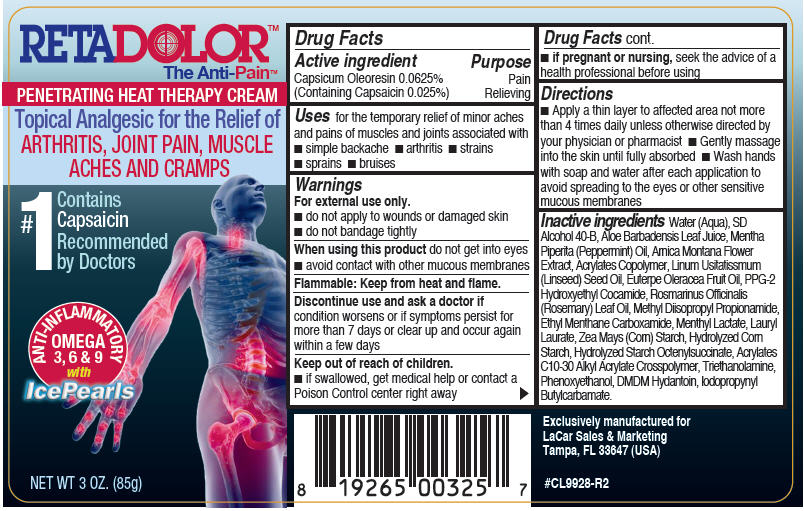 DRUG LABEL: RETADOLOR 
NDC: 69279-144 | Form: CREAM
Manufacturer: LACAR SALES & MARKETING INC.
Category: otc | Type: HUMAN OTC DRUG LABEL
Date: 20150821

ACTIVE INGREDIENTS: Capsaicin 0.25 mg/1 g
INACTIVE INGREDIENTS: Water; ARNICA MONTANA FLOWER; METHYL DIISOPROPYL PROPIONAMIDE; LAURYL LAURATE; PHENOXYETHANOL; DMDM HYDANTOIN; IODOPROPYNYL BUTYLCARBAMATE; ALOE VERA LEAF; MENTHYL LACTATE, (-)-; STARCH, CORN; PPG-2 HYDROXYETHYL COCAMIDE; TROLAMINE; ALCOHOL; PEPPERMINT OIL; LINSEED OIL; ACAI OIL; ETHYL MENTHANE CARBOXAMIDE; ROSEMARY OIL

RETADOLOR™
Pain Relief

Drug Facts

Active ingredient

Capsicum Oleoresin 0.0625% (Containing Capsaicin 0.025%)

Purpose

Pain Relieving

Uses

for the temporary relief of minor aches and pains of muscles and joints associated with

- simple backache
- arthritis
- strains
- sprains
- bruises

Warnings

For external use only.

- do not apply to wounds or damaged skin
- do not bandage tightly

When using this product do not get into eyes

- avoid contact with other mucous membranes

Flammable

Keep from heat and flame.

ASK DOCTOR

Discontinue use and ask a doctor if condition worsens or if symptoms persist for more than 7 days or clear up and occur again within a few days

Keep out of reach of children.

- if swallowed, get medical help or contact a Poison Control center right away

PREGNANCY OR BREAST FEEDING

- if pregnant or nursing, seek the advice of a health professional before using

Directions

- Apply a thin layer to affected area not more than 4 times daily unless otherwise directed by your physician or pharmacist
- Gently massage into the skin until fully absorbed
- Wash hands with soap and water after each application to avoid spreading to the eyes or other sensitive mucous membranes

Inactive ingredients

Water (Aqua), SD Alcohol 40-B, Aloe Barbadensis Leaf Juice, Mentha Piperita (Peppermint) Oil, Arnica Montana Flower Extract, Acrylates Copolymer, Linum Usitatissmum (Linseed) Seed Oil, Euterpe Oleracea Fruit Oil, PPG-2 Hydroxyethyl Cocamide, Rosmarinus Officinalis (Rosemary) Leaf Oil, Methyl Diisopropyl Propionamide, Ethyl Menthane Carboxamide, Menthyl Lactate, Lauryl Laurate, Zea Mays (Corn) Starch, Hydrolyzed Corn Starch, Hydrolyzed Starch Octenylsuccinate, Acrylates C10-30 Alkyl Acrylate Crosspolymer, Triethanolamine, Phenoxyethanol, DMDM Hydantoin, Iodopropynyl Butylcarbamate.

PRINCIPAL DISPLAY PANEL - 85 g Bottle Label

RETADOLOR™
The Anti-Pain™

PENETRATING HEAT THERAPY CREAM

Topical Analgesic for the Relief of
ARTHRITIS, JOINT PAIN, MUSCLE
ACHES AND CRAMPS

#1
Contains
Capsaicin
Recommended
by Doctors

ANTI-INFLAMMATORY
OMEGA
3, 6 & 9
with
IcePearls

NET WT 3 OZ. (85g)